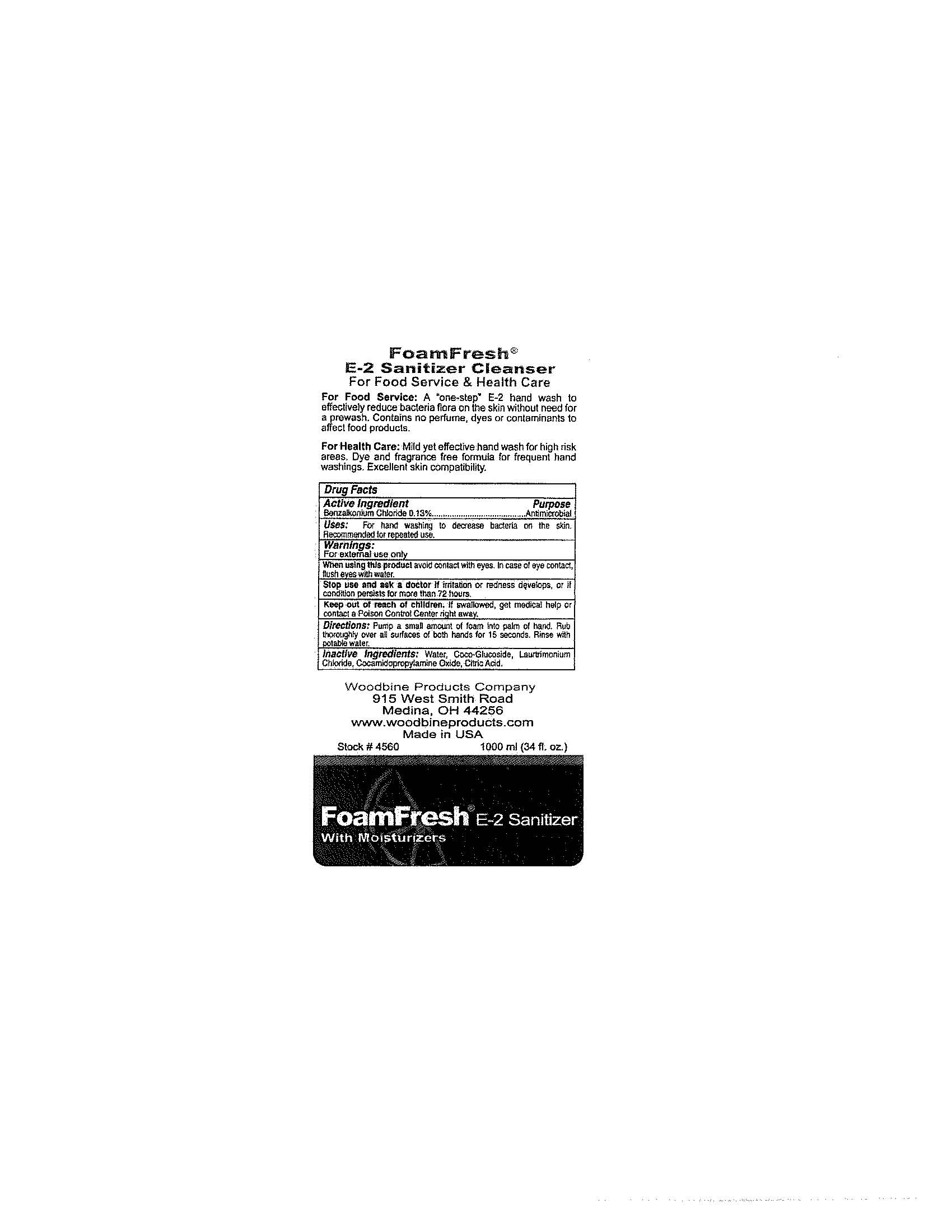 DRUG LABEL: FoamFresh E-2 Sanitizer Cleanser
NDC: 11429-1002 | Form: LIQUID
Manufacturer: Woodbine Products Company
Category: otc | Type: HUMAN OTC DRUG LABEL
Date: 20241125

ACTIVE INGREDIENTS: BENZALKONIUM CHLORIDE 1.3 mg/1 mL
INACTIVE INGREDIENTS: WATER; COCO GLUCOSIDE; LAURTRIMONIUM CHLORIDE; COCAMIDOPROPYLAMINE OXIDE; CITRIC ACID MONOHYDRATE

Drug Facts 11429-1002

Active Ingredient

Benzalkonium Chloride 0.13%

Purpose

Antimicrobial

Uses:

For hand washing to decrease bacteria on the skin.

Recommended for repeated use.

Warnings:

For external use only

When using this product avoid contact with eyes.

In case of eye contact, flush with water.

Stop use and ask a doctor if irritation or redness develops, or if condition persists for more than 72 hours.

Keep out of reach of children.

If swallowed, get medical help or contact a Poison Control Center right away.

Directions:

Pump a small amount of foam into palm of hand.

Rub thoroughly over all surfaces of both hands for 15 seconds.

Rinse with potable water.

Inactive Ingredients:

Water, Coco-Glucoside, Laurtrimonium Chloride, Cocamidopropylamine Oxide, Citric Acid.

PACKAGE LABEL

FoamFresh

E-2 Sanitizer Cleanser

For Food Service and Health Care

For Food Service:

A "one-step" E-2 hand wash to effectively reduce bacteria flora on the skin without need for a prewash.

Contains no perfume, dyes or contaminants to affect food products.

For Health Care:

Mild yet effective hand wash for high risk areas.

Dye and fragrance free formula for frequent hand washings.

Excellent skin compatibility.

Woodbine Products Company

915 West Smith Road

Medina, OH 44256

www.woodbineproducts.com

Made in USA

Stock # 4560 1000 ml (34 fl. oz.)

FoamFresh E-2 Sanitizer

With Moisturizers